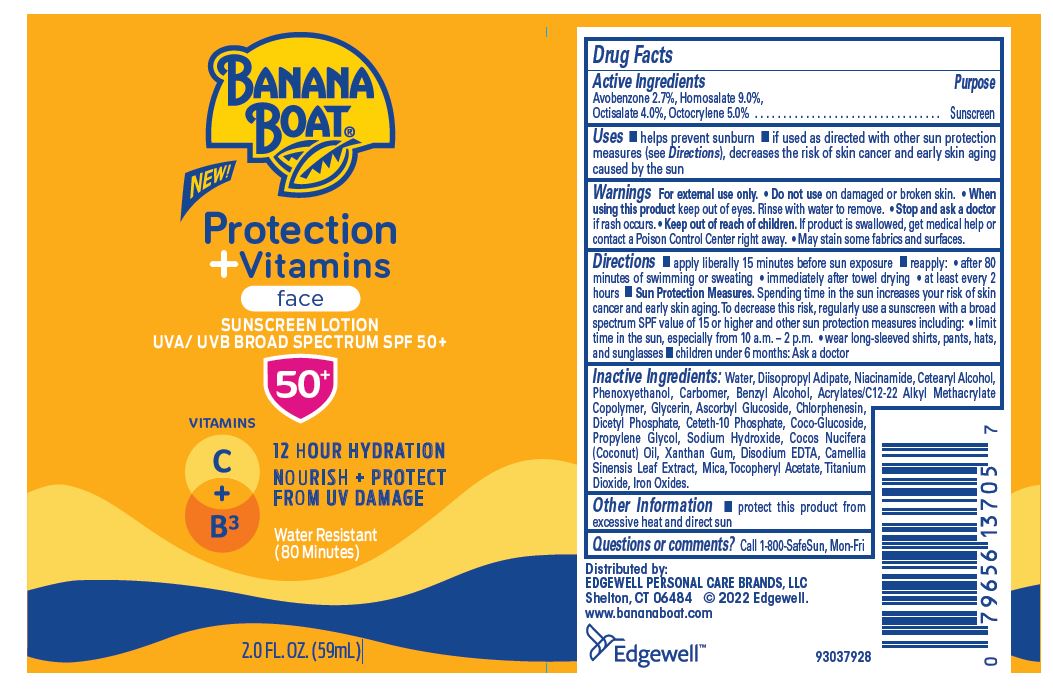 DRUG LABEL: BANANA BOAT PROTECTION PLUS VITAMINS FACE SUNSCREEN UVA/UVB BROAD SPECTRUM SPF 50
NDC: 63354-500 | Form: LOTION
Manufacturer: Edgewell Personal Care Brands LLC
Category: otc | Type: HUMAN OTC DRUG LABEL
Date: 20251117

ACTIVE INGREDIENTS: OCTOCRYLENE 5 g/100 g; OCTISALATE 4 g/100 g; AVOBENZONE 2.7 g/100 g; HOMOSALATE 9 g/100 g
INACTIVE INGREDIENTS: PHENOXYETHANOL; XANTHAN GUM; COCO GLUCOSIDE; DIISOPROPYL ADIPATE; MICA; ASCORBYL GLUCOSIDE; FERRIC OXIDE YELLOW; TITANIUM DIOXIDE; SODIUM HYDROXIDE; GREEN TEA LEAF; NIACINAMIDE; PROPYLENE GLYCOL; COCONUT OIL; .ALPHA.-TOCOPHEROL ACETATE; DIHEXADECYL PHOSPHATE; WATER; CETOSTEARYL ALCOHOL; BENZYL ALCOHOL; GLYCERIN; CETETH-10 PHOSPHATE; EDETATE DISODIUM; CHLORPHENESIN

Active Ingredients

Avobenzone 2.7%, Homosalate 9.0%, Octisalate 4.0%, Octocrylene 5.0% .

Purpose

Sunscreen

Uses

- helps prevent sunburn
- if used as directed with other sun protection measures (see Directions), decreases the risk of skin cancer and early skin aging

caused by the sun

Warnings

For external use only.

• May stain some fabrics and surfaces.

When sing this product

keep out of eyes. Rinse with water to remove.

Do not use

on damaged or broken skin.

Stop and ask a doctor

if rash occurs.

Keep out of reach of children.

If product is swallowed, get medical help or contact a Poison Control Center right away.

Directions

- apply liberally 15 minutes before sun exposure • reapply: • after 80 minutes of swimming or sweating • immediately after towel drying • at least every 2 hours • Sun Protection Measures. Spending time in the sun increases your risk of skin cancer and early skin aging. To decrease this risk, regularly use a sunscreen with a broad spectrum SPF value of 15 or higher and other sun protection measures including: • limit time in the sun, especially from 10 a.m. – 2 p.m. • wear long-sleeved shirts, pants, hats, and sunglasses • children under 6 months: Ask a doctor

Inactive Ingredients

Water, Diisopropyl Adipate, Niacinamide, Cetearyl Alcohol, Phenoxyethanol, Carbomer, Benzyl Alcohol, Acrylates/C12-22 Alkyl Methacrylate Copolymer, Glycerin, Ascorbyl Glucoside, Chlorphenesin, Dicetyl Phosphate, Ceteth 10 Phosphate, Coco Glucoside,
Propylene Glycol, Sodium Hydroxide, Cocos Nucifera (Coconut) Oil, Xanthan Gum, Disodium EDTA, Camellia Sinensis Leaf Extract, Mica, Tocopheryl Acetate, Titanium Dioxide, Iron Oxides.

Other Information

protect this product from excessive heat and direct sun

Questions or comments?

Call 1-800-SafeSun, Mon-Fri

PRINCIPAL DISPLAY PANEL

BANANA

BOAT

NEW!

Protection

+ Vitamins

face

SUNSCREEN LOTION
UVA/ UVB BROAD SPECTRUM SPF 50+

50+

VITAMINS

C + B3

12 HOUR HYDRATION
NOURISH + PROTECT
FROM UV DAMAGE

Water Resistant
(80 Minutes)

2.0 FL. OZ. (59mL)